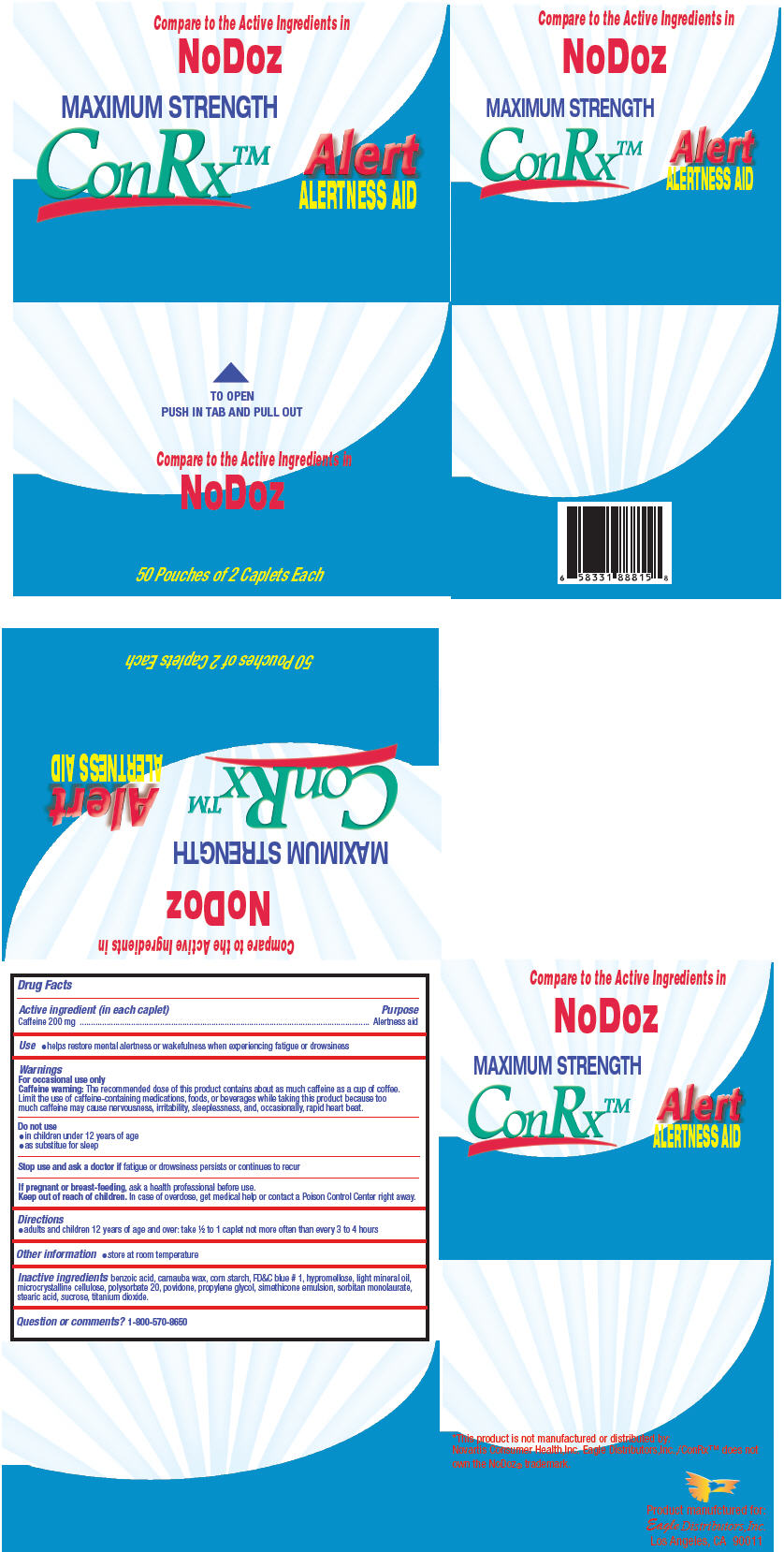 DRUG LABEL: ConRx Alert
NDC: 68737-229 | Form: TABLET
Manufacturer: Eagle Distributors,Inc.
Category: otc | Type: HUMAN OTC DRUG LABEL
Date: 20130211

ACTIVE INGREDIENTS: Caffeine 200 mg/1 1
INACTIVE INGREDIENTS: BENZOIC ACID; CARNAUBA WAX; STARCH, CORN; FD&C BLUE NO. 1; HYPROMELLOSES; LIGHT MINERAL OIL; CELLULOSE, MICROCRYSTALLINE; POLYSORBATE 20; POVIDONES; POLYETHYLENE GLYCOL 6000; DIMETHICONE; SORBITAN MONOLAURATE; STEARIC ACID; SUCROSE; TITANIUM DIOXIDE

ConRx™ Alert

Drug Facts

Active ingredient (in each caplet)

Caffeine 200 mg

Purpose

Alertness aid

Use

♦ helps restore mental alertness or wakefulness when experiencing fatigue or drowsiness

Warnings

For occasional use only

Caffeine warning

The recommended dose of this product contains about as much coffeube as a cup of coffee. Limit the use of caffeine-containing medications, foods, or beverages while taking this product because too much caffeine may cause nervousness, irritability, sleeplessness, and, occasionally, rapid heart beat.

Do not use

♦ in children under 12 years of age
♦ as substitue for sleep

Stop use and ask a doctor if fatigue or drowsiness persists or continues to recur

PREGNANCY OR BREAST FEEDING

If pregnant or breast-feeding, ask a health professional before use.

Keep out of reach of children. In case of overdose, get medical help or contact a Poison Control Center right away

Directions

♦ adults and children 12 years of age and over: take ½ to 1 caplet not more often than every 3 to 4 hours

Other information

♦ store at room temperature

Inactive ingredients

benzoic acid, carnauba wax, corn starch, FD&C blue # 1, hypromellose, light mineral oil, microcrystalline cellulose, polysorbate 20, povidone, propylene glycol, simethicone emulsion, sorbitan monolaurate, stearic acid, sucrose,titanium dioxide.

Question or comments?

1-800-570-8650

PRINCIPAL DISPLAY PANEL - 50 Pouch Box

Compare to the Active Ingredients in
NoDoz

MAXIMUM STRENGTH
ConRx™

Alert
ALERTNESS AID

TO OPEN
PUSH IN TAB AND PULL OUT

Compare to the Active Ingredients in
NoDoz

50 Pouches of 2 Caplets Each